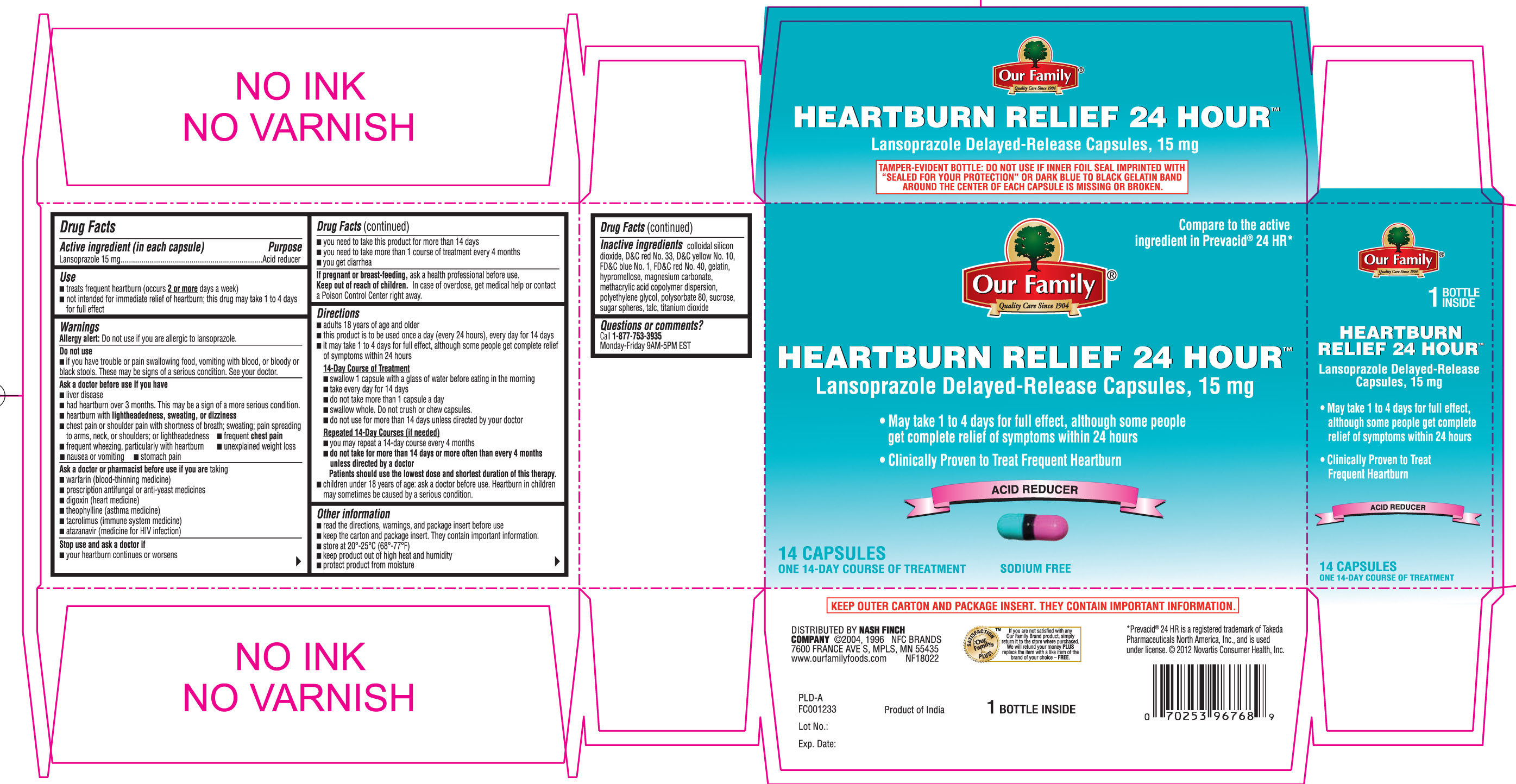 DRUG LABEL: Heartburn Relief 24 hour
NDC: 70253-019 | Form: CAPSULE, DELAYED RELEASE
Manufacturer: OUR FAMILY (Nash Finch Company)
Category: otc | Type: HUMAN OTC DRUG LABEL
Date: 20130416

ACTIVE INGREDIENTS: LANSOPRAZOLE 15 mg/1 1
INACTIVE INGREDIENTS: D&C RED NO. 33; D&C YELLOW NO. 10; FD&C BLUE NO. 1; FD&C RED NO. 40; GELATIN; HYPROMELLOSES; MAGNESIUM CARBONATE; POLYETHYLENE GLYCOLS; POLYSORBATE 80; SILICON DIOXIDE; STARCH, CORN; SUCROSE; TALC; TITANIUM DIOXIDE; METHACRYLIC ACID - METHYL METHACRYLATE COPOLYMER (1:1)

DRUG FACTS

Active ingredient (in each capsule)

Lansoprazole 15 mg

Purpose

Acid reducer

Use

- treats frequent heartburn (occurs 2 or more days a week)
- not intended for immediate relief of heartburn; this drug may take 1 to 4 days for full effect

WARNINGS

Allergy alert: Do not use if you are allergic to lansoprazole

Do not use

- if you have trouble or pain swallowing food, vomiting with blood, or bloody or black stools. These may be signs of a serious condition. See your doctor.

Ask a doctor before use if you have

- liver disease
- had heartburn over 3 months. This may be a sign of a more serious condition.
- heartburn with lightheadedness, sweating or dizziness
- chest pain or shoulder pain with shortness of breath; sweating; pain spreading to arms, neck or shoulders; or lightheadedness
- frequent chest pain
- frequent wheezing, particularly with heartburn
- unexplained weight loss
- nausea or vomiting
- stomach pain

Ask a doctor or pharmacist before use if you are taking

- warfarin (blood-thinning medicine)
- prescription antifungal or anti-yeast medicines
- digoxin (heart medicine)
- theophylline (asthma medicine)
- tacrolimus (immune system medicine)
- atazanavir (medicine for HIV infection)

Stop use and ask a doctor if

- your heartburn continues or worsens
- you need to take this product for more than 14 days
- you need to take more than 1 course of treatment every 4 months
- you get diarrhea

If pregnant or breast-feeding

ask a health professional before use.

Keep out of reach of children

In case of overdose, get medical help or contact a Poison Control Center right away.

Directions

- adults 18 years of age and older
- this product is to be used once a day (every 24 hours), every day for 14 days
- it may take 1 to 4 days for full effect, although some people get complete relief of symptoms within 24 hours

14-Day Course of Treatment

- swallow 1 capsule with a glass of water before eating in the morning
- take every day for 14 days
- do not take more than 1 capsule a day
- swallow whole. Do not crush or chew capsules.
- do not use for more than 14 days unless directed by your doctor

Repeated 14-Day Courses (if needed)

- you may repeat a 14-day course every 4 months
- do not take for more than 14 days or more often than every 4 months unless directed by a doctor. Patients should use the lowest dose and shortest duration of this therapy.
- children under 18 years of age: ask a doctor before use. Heartburn in children may sometimes be caused by a serious condition.

Other information

- read the directions, warnings and package insert before use
- keep the carton and package insert. They contain important information.
- store at 20°-25°C (68°-77°F)
- keep product out of high heat and humidity
- protect product from moisture

Inactive ingredients

colloidal silicon dioxide, D & C Red No. 33, D & C Yellow No. 10, FD & C Blue No. 1, FD & C Red No. 40, gelatin, hypromellose, magnesium carbonate, methacrylic acid copolymer dispersion, polyethylene glycol, polysorbate 80, sucrose, sugar spheres, talc, titanium dioxide

Questions or comments?

Call 1-877-753-3935 Monday-Friday 9AM-5PM EST

Principal Display Panel

Compare to the active ingredient in Prevacid® 24 HR*

*Prevacid® 24 HR is a registered trademark of Takeda Pharmaceuticals North America, Inc., and is used under license. ©2012 Novartis Consumer Health. Inc

HEARTBURN RELIEF 24 HOUR™

Lansoprazole Delayed- Release capsules, 15 mg

- may take 1 to 4 days for full effect, although some people get complete relief of symptoms within 24 hours
- Clinically proven to treat frequent heartburn

ACID REDUCER

Sodium Free

Product of India

KEEP OUTER CARTON AND PACKAGE INSERT. THEY CONTAIN IMPORTANT INFORMATION.

TAMPER-EVIDENT BOTTLE: DO NOT USE IF INNER FOIL SEAL IMPRINTED WITH “SEALED for YOUR PROTECTION” OR DARK BLUE TO BLACK GELATIN BAND AROUND THE CENTER OF EACH CAPSULE IS MISSING OR BROKEN.

Product Label

Lansoprazole delayed release capsules 15 mg